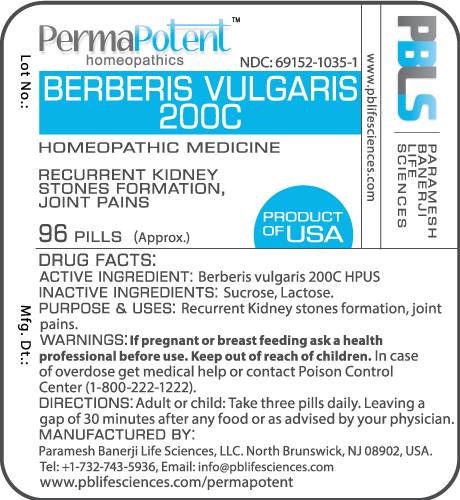 DRUG LABEL: Berberis vulgaris 200C
NDC: 69152-1035 | Form: PELLET
Manufacturer: Paramesh Banerji Life Sciences LLC
Category: homeopathic | Type: HUMAN OTC DRUG LABEL
Date: 20160428

ACTIVE INGREDIENTS: BERBERIS VULGARIS ROOT BARK 200 [hp_C]/1 1
INACTIVE INGREDIENTS: SUCROSE; LACTOSE

DRUG FACTS: Active Ingredient

Berberis vulgaris 200C HPUS

Inactive Ingredients

Sucrose, Lactose

Purpose

Recurrent kidney stones formation, joint pains

Uses

Recurrent kidney stones formation, joint pains

Warnings

If pregnant or breast feeding ask a health professional before use.

Keep out of reach of children. In case of overdose, get medical help or contact a Poison Control Center (1-800-222-1222) right away.

Direction

Adult or child: Take three pills daily. Leaving a gap of 30 minutes after any food or as advised by your physician.

Manufactured by

Paramesh Banerji Life Sciences, LLC.

North Brunswick, NJ 08902, USA.

Tel: +1-732-743-5936,

Email: info@pblifesciences.com

www.pblifesciences.com/permapotent

Principal Display Panel

NDC: 69152-1035-1

Berberis vulgaris 200C

Homeopathic Medicine

Recurrent kidney stones formation, joint pains

96 Pills (Approx.)

Product of USA